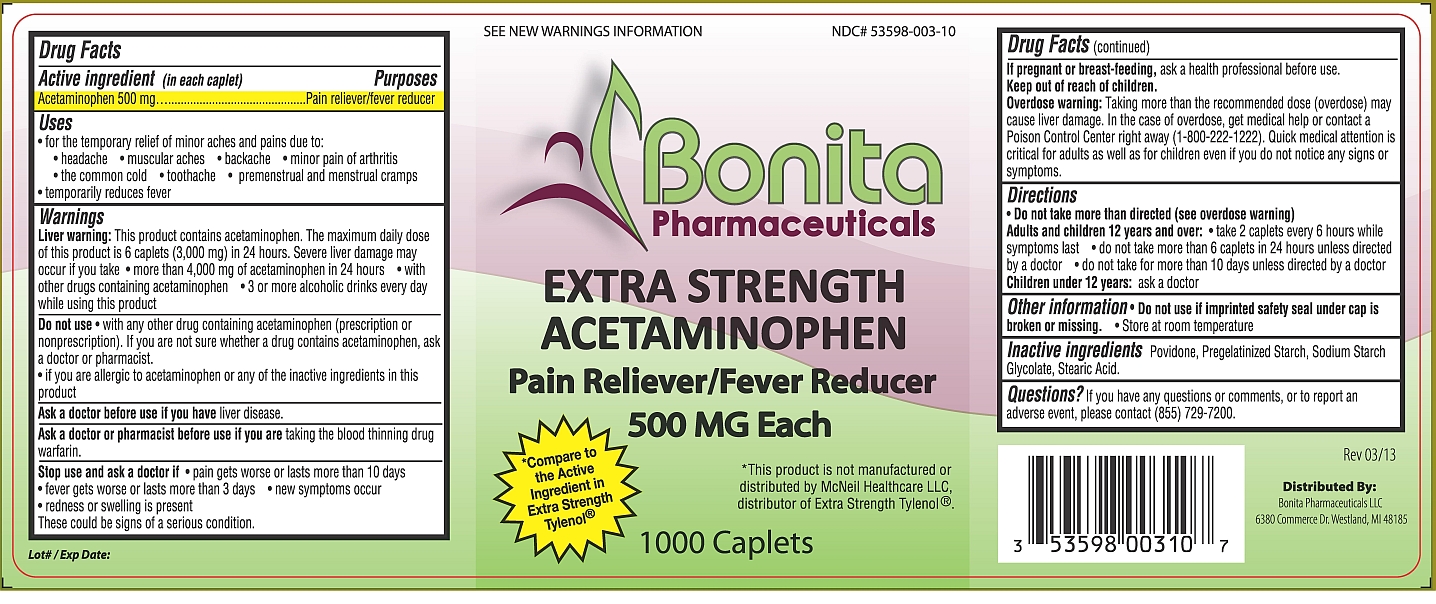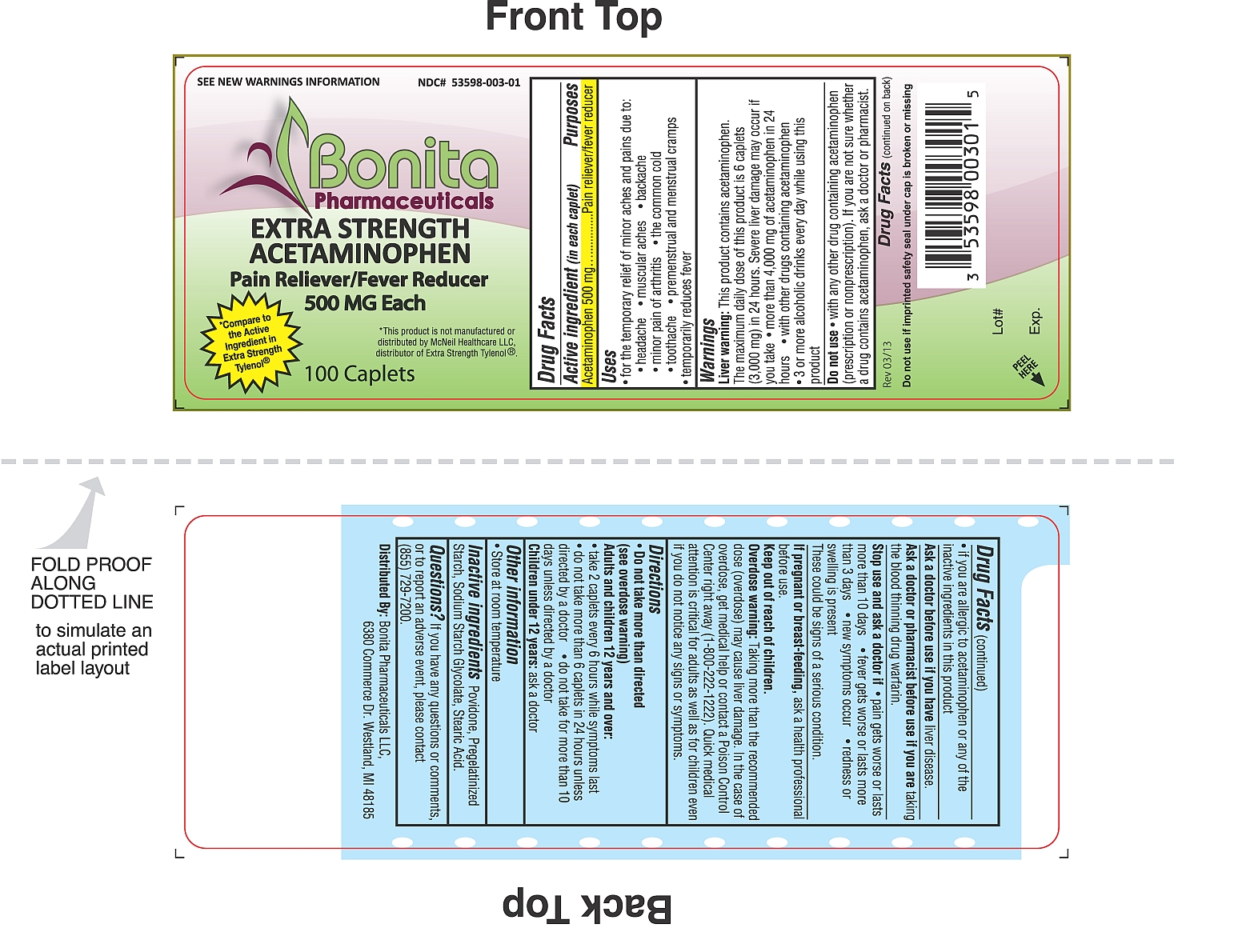 DRUG LABEL: Acetaminophen
NDC: 53598-003 | Form: TABLET, COATED
Manufacturer: Bonita Pharmaceuticals LLC
Category: otc | Type: HUMAN OTC DRUG LABEL
Date: 20130402

ACTIVE INGREDIENTS: ACETAMINOPHEN 500 mg/1 1
INACTIVE INGREDIENTS: POVIDONE; STARCH, PREGELATINIZED CORN; SODIUM STARCH GLYCOLATE TYPE A CORN; STEARIC ACID

Extra Strength Acetaminophen 500mg Caplets

Active Ingredient

(in each caplet)

Acetaminophen 500mg

Purposes

Pain reliever/Fever reducer

Uses

For the temporary relief of minor aches and pains due to:

- Headache
- Muscular aches
- Backache
- Minor pain of arthritis
- The common cold
- Toothache
- Premenstrual and menstrual cramps

Temporarily reduces fever.

Warnings

Liver warning:

This product contains acetaminophen. The maximum daily dose of this product is 6 caplets (3,000mg) in 24 hours. Severe liver damage may occur if you take

- more than 4,000mg of acetaminophen in 24 hours
- with other drugs containing acetaminophen
- 3 or more alcoholic drinks every day while using this product

Do not use

- with any other drug containing acetaminophen (prescription or nonprescription). If you are not sure whether a drug contains acetaminophen, ask a doctor or pharmacist.
- if you are allergic to acetaminophen or any of the inactive ingredients in this product

Ask a doctor before use if you have

liver disease.

Ask a doctor or pharmacist before use if you are

taking the blood thinning drug warfarin.

Stop use and ask a doctor if

- pain gets worse or lasts more than 10 days
- fever gets worse or lasts more than 3 days
- new symptoms occur
- redness or swelling is pressent

These could be signs of a serious condition.

If pregnant or breast-feeding,

ask a health professional before use.

Keep out of reach of children.

Overdose warning:

Taking more than the recommended dose (overdose) may cause liver damage. In case of overdose, get medical help or contact a Poison Control Center right away (1-800-222-1222). Quick medical attention is critical for adults as well as for children even if you do not notice any signs or symptoms.

Directions

- Do not take more than directed (see overdose warning)

Adults and children 12 years and over:

- take 2 caplets every 6 hours while symptoms last
- do not take more than 6 caplets in 24 hours unless directed by a doctor
- do not take for more than 10 days unless directed by a doctor

Children under 12 years: ask a doctor

Other Information

- Do not use if imprinted safety seal under cap is broken or missing
- Store at room temperature

Inactive Ingredients

- Povidone
- Pregelatinized Starch
- Sodium Starch Glycolate
- Stearic Acid

Questions?

If you have any questions or comments, or to report an adverse event, please contact (855) 729-7200.

PRINCIPAL DISPLAY PANEL

Image 1 : Extra Strength Acetaminophen 500mg, 1000ct caplets

Image 2 : Extra Strength Acetaminophen 500mg, 100ct caplets